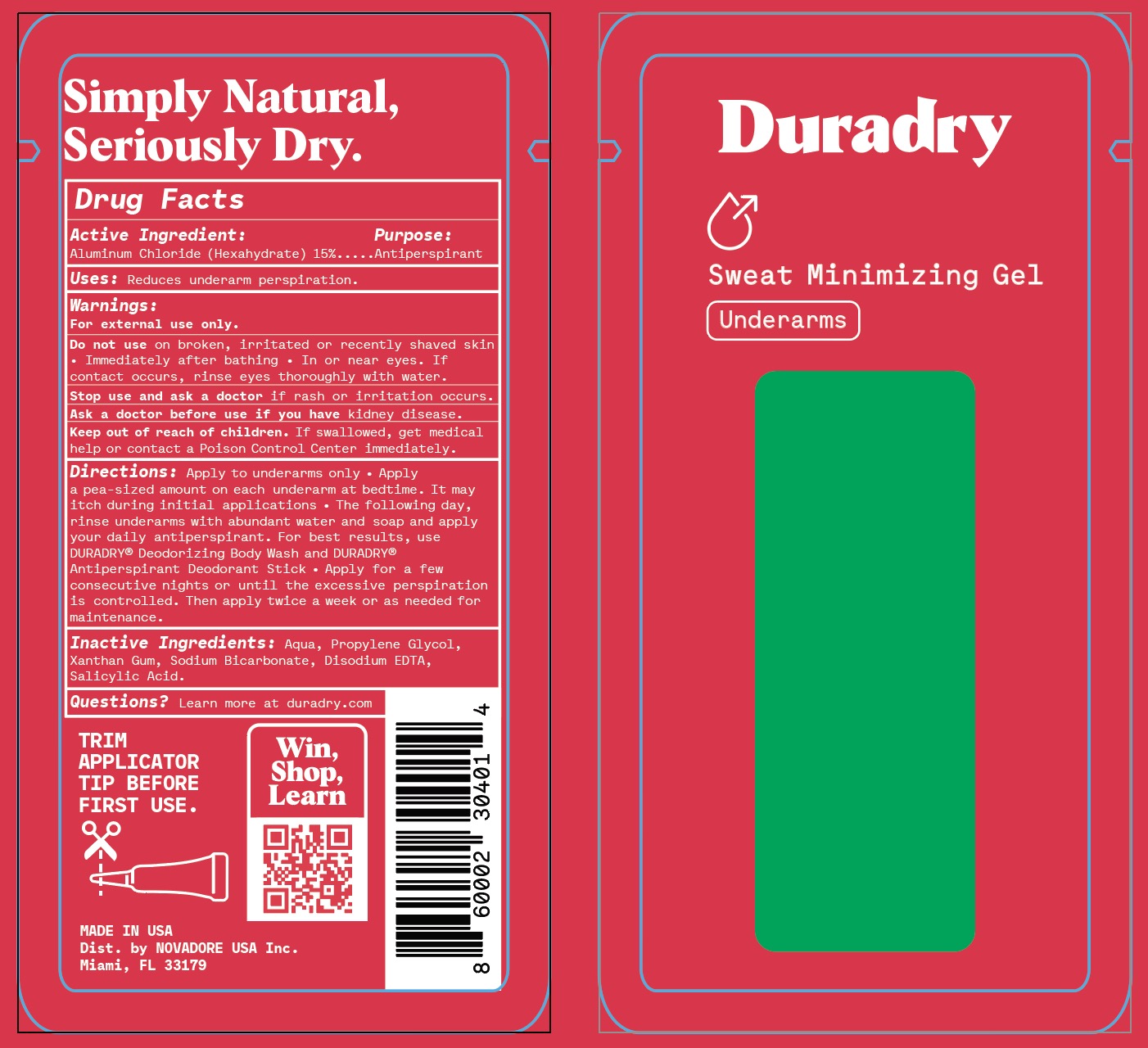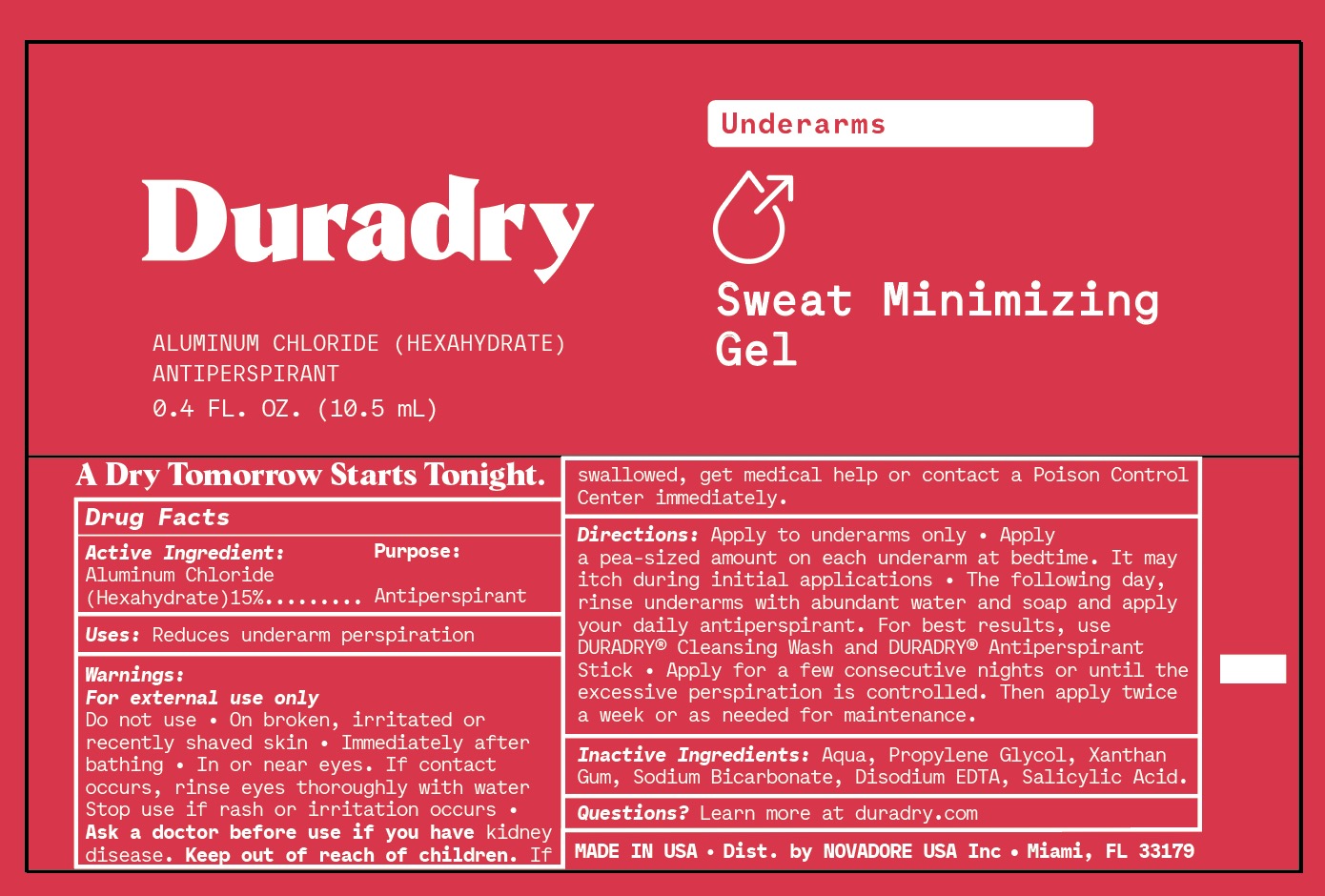 DRUG LABEL: Duradry Sweat Minimizing Gel
NDC: 69990-103 | Form: GEL
Manufacturer: Novadore USA Inc
Category: otc | Type: HUMAN OTC DRUG LABEL
Date: 20251111

ACTIVE INGREDIENTS: ALUMINUM CHLORIDE 150 mg/1 mL
INACTIVE INGREDIENTS: EDETATE DISODIUM; PROPYLENE GLYCOL; WATER; XANTHAN GUM; SALICYLIC ACID; SODIUM BICARBONATE

Duradry Sweat Minimizing Gel

Active ingredient

ALUMINUM CHLORIDE (HEXAHYDRATE) 15%

Purpose

Antiperspirant

Uses

Reduces underarm perspiration

Warnings

For external use only
Stop use if rash or irritation occurs.

Do not use

- On broken, irritated or recently shaved skin.
- Immediately after bathing.
- In or near eyes. If contact occurs, rise eyes thoroughly with water.

Ask a doctor before use

if you have kidney disease

Keep out of reach of children

If swallowed, get medical help or contact a Poison Control Center right away.

Directions

- Apply to underarms only.
- Apply a small amount of product to underarms at bedtime. It may itch during initial application.
- The next morning, rinse underarms with abundant water and apply a regular antiperspirant. For best results, use DURADRY® AM.
- Apply DURADRY® PM for a few nights in a row or until the excessive perspiration is controlled. Then Apply twice a week or as needed for maintenance.

Inactive ingredients

Aqua, Propylene Glycol, Xanthan Gum, Sodium Bicarbonate,Disodium EDTA, Salicylic Acid.

Questions?

Learn more at duradry.com